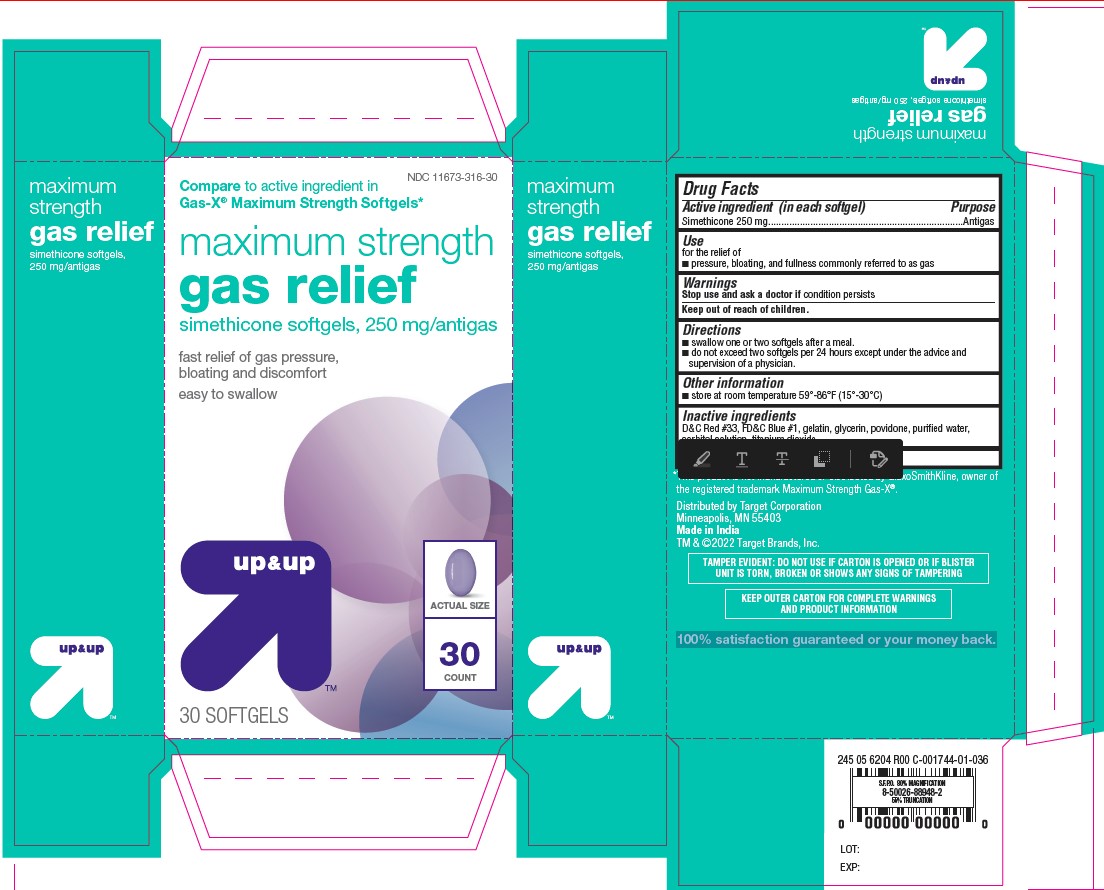 DRUG LABEL: maxumim strength gas relief simethicone softgel 250 mg
NDC: 11673-316 | Form: CAPSULE, LIQUID FILLED
Manufacturer: Target Corporation
Category: otc | Type: HUMAN OTC DRUG LABEL
Date: 20241230

ACTIVE INGREDIENTS: DIMETHICONE 250 mg/1 1
INACTIVE INGREDIENTS: TITANIUM DIOXIDE; GELATIN; GLYCERIN; SORBITOL SOLUTION 70%; POVIDONE K30; FD&C BLUE NO. 1; D&C RED NO. 33; WATER

maxumim strength gas relief simethicone softgel 250 mg

Active ingredient (in each softgel)

Simethicone 250 mg

Purpose

Antigas

Use

for the relief of

- pressure, bloating, and fullness commonly referred to as gas

Stop use and ask a doctor

if condition persists

Directions

- swallow one or two softgels after a meal.
- do not exceed two softgels per 24 hours except under the advice and supervision of a physician.

Other information

- store at room temperature 59°-86°F (15°-30°C)

Inactive ingredients

D&C Red #33, FD&C Blue #1, gelatin, glycerin, povidone, purified water,
sorbitol solution, titanium dioxide

Questions or comments?

1-888-333-9792

Carton

*This product is not manufactured or distributed by GlaxoSmithKline, owner of
the registered trademark Maximum Strength Gas-X®.

Distributed by Target Corporation
Minneapolis, MN 55403
Made in India
TM & ©2022 Target Brands, Inc.

TAMPER EVIDENT: DO NOT USE IF CARTON IS OPENED OR IF BLISTER
UNIT IS TORN, BROKEN OR SHOWS ANY SIGNS OF TAMPERING

KEEP OUTER CARTON FOR COMPLETE WARNINGS
AND PRODUCT INFORMATION

100% satisfaction guaranteed or your money back.

Carton